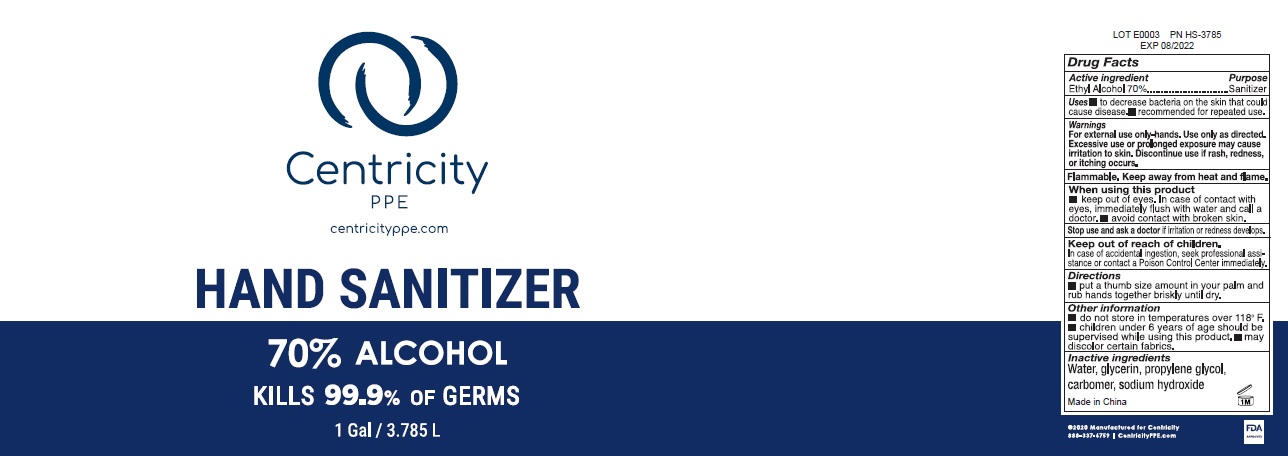 DRUG LABEL: Centricity/STAR Products Hand Sanitizer
NDC: 74274-018 | Form: LIQUID
Manufacturer: Huizhou Bliss Commodity Co., Ltd
Category: otc | Type: HUMAN OTC DRUG LABEL
Date: 20200721

ACTIVE INGREDIENTS: ALCOHOL 70 mL/100 mL
INACTIVE INGREDIENTS: WATER; GLYCERIN; PROPYLENE GLYCOL; SODIUM HYDROXIDE

Drug Facts

Ethyl Alcohol .............. 70%

Purpose

Sanitizer

Use

- To decreases bacteria on the skin that could cause disease
- Recommended for repeated use.

Warnings

- For external use only-hands. Use only as directed.
- Flammable, keep away fro heat and flame.

Excessive use or prolonged exposure may cause irritation to skin.

Discontinue use if rash, redness, or itching occurs.

When using this product

- Keep out of eyes. In case of contact with eyes, immediately flush with water and call a doctor
- avoid contact with broken skin.

Other Information:

- do not store in temperatures over 118℉
- children under 6 years of age should be supervised while using this product.
- may discolor certain fabrics.

In case of accidental ingestion, seek professional assistance or contact poison control Center immediately.

If swallowed, get medical help or contact a Poison Control Center right away.

Directions

put a thumb size amount into your palm and rub hands together until dry.

Inactive ingredients

Water, glycerin, propyene glycol, carbomer, sodium hydroxide